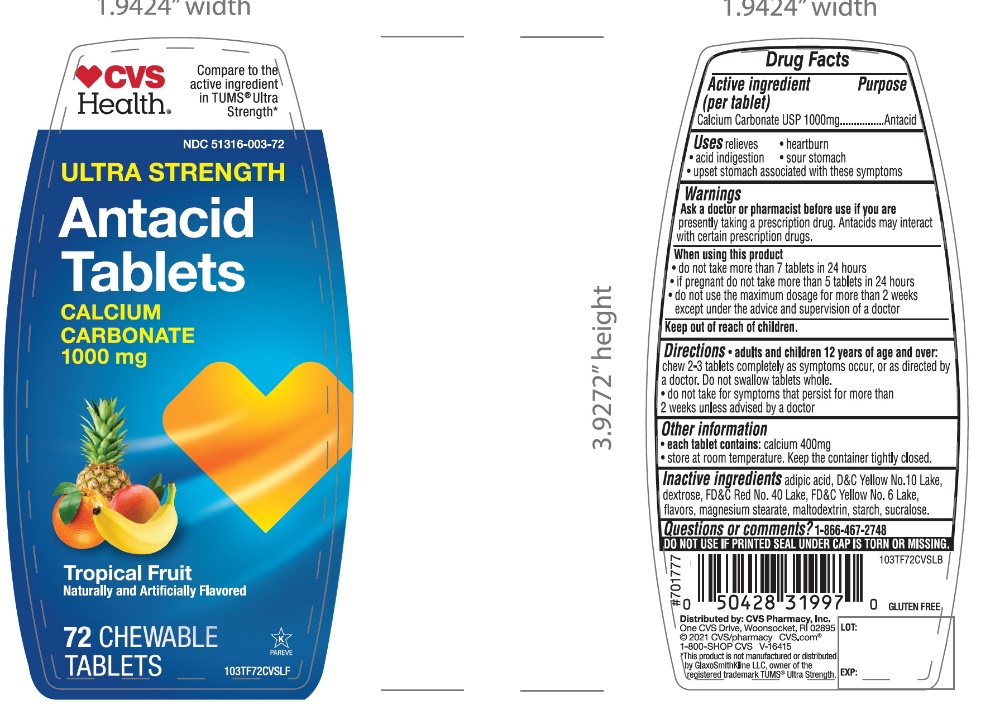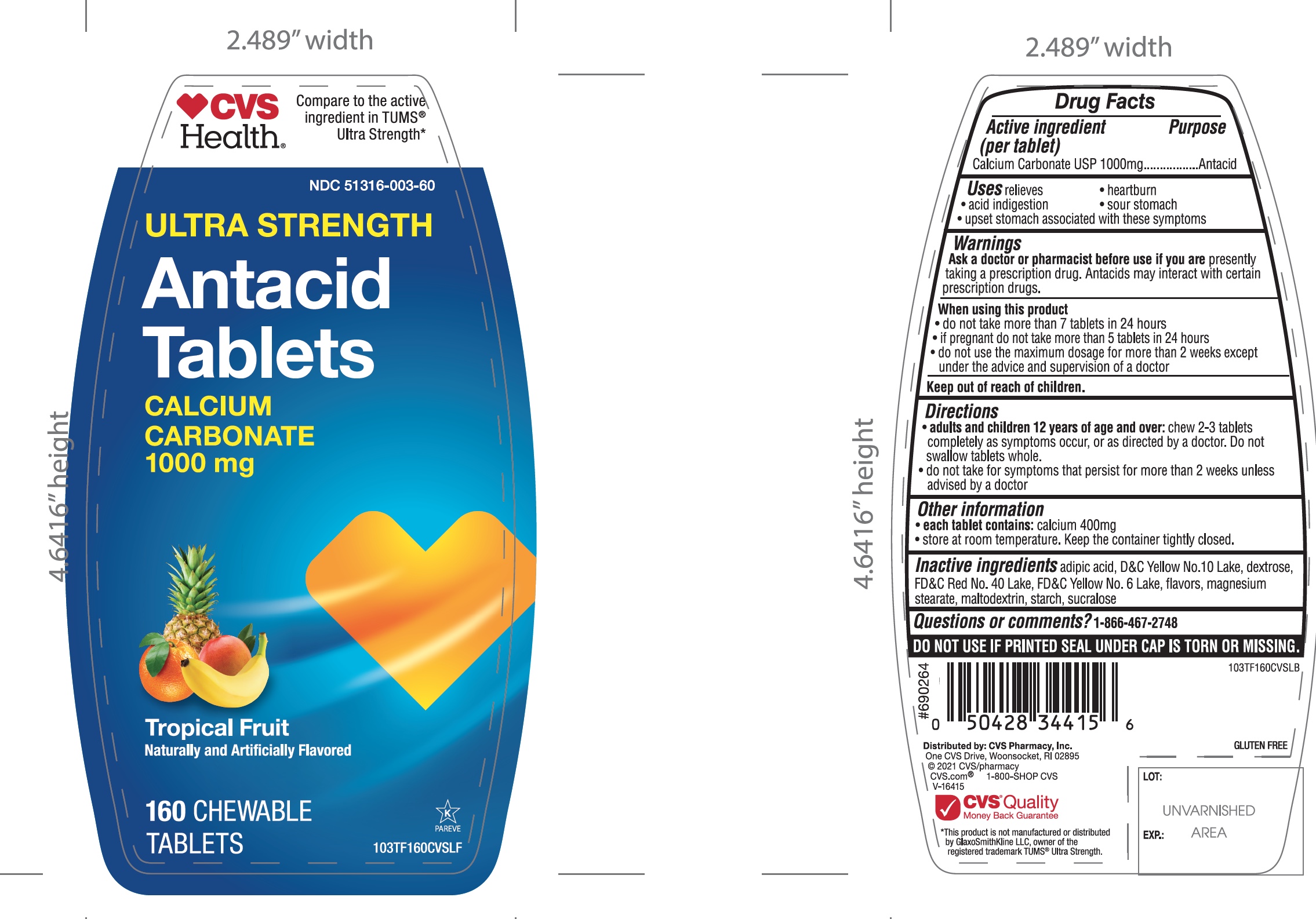 DRUG LABEL: CVS

NDC: 51316-003 | Form: TABLET, CHEWABLE
Manufacturer: CVS
Category: otc | Type: HUMAN OTC DRUG LABEL
Date: 20251204

ACTIVE INGREDIENTS: CALCIUM CARBONATE 1000 mg/1 1
INACTIVE INGREDIENTS: ADIPIC ACID; D&C YELLOW NO. 10; DEXTROSE, UNSPECIFIED FORM; FD&C RED NO. 40; FD&C YELLOW NO. 6; MAGNESIUM STEARATE; MALTODEXTRIN; STARCH, CORN; SUCRALOSE

CVS ultra-strength antacid calcium carbonate Tropical Fruit 72 Chewable Tablets

Active ingredient (per tablet)

Calcium Carbonate USP 1000mg

Purpose

Antacid

Uses

relieves

- heartburn
- acid indigestion
- sour stomach
- upset stomach associated with these symptoms

Warnings

Ask a doctor or pharmacist before use if you arepresently taking a prescription drug. Antacids may interact with certain prescription drugs.

When using this product

- do not take more than 7 tablets in 24 hours
- if pregnant do not take more than 5 tablets in 24 hours
- do not use the maximum dosage for more than 2 weeks except under the advice and supervision of a doctor.

Directions

- adults and children 12 years of age and over:chew 2-3 tablets as symptoms occur, or as directed by a doctor. Do not swallow tablets as whole
- do not take for symptoms that persist for more than 2 weeks unless advised by a doctor

Other information

- each tablet contains: calcium 400mg
- store at room temperature. Keep the container tightly closed

Inactive ingredients

adipic acid, D&C yellow 10 lake, dextrose, FD&C Red 40 lake, FD&C yellow 6 lake, flavors, magnesium stearate, maltodextrin, starch, sucralose

Questions?

1-866-467-2748

Safety sealed: Do not use if printed seal under cap is torn or missing

Package/Label Principal Display Panel

NDC 51316-003-72

*Compare to active ingredient in Ultra Strength Tums®

Ultra Strength

Antacid Tablets

Calcium Ccarbonate 1000 mg

Fast Relief of Upset Stomach, Heartburn, and Acid Indigestion

Tropical Fruit

Naturally and Artificially flavored

72 CHEWABLE TABLETS

Gluten- Free

Distributed By

*This product is not manufactured or distributed by GlaxoSmithKline LLC, owner of the registered trademark, Ultra Strength Tums®.

Package Label for 72 Chewable Tablets